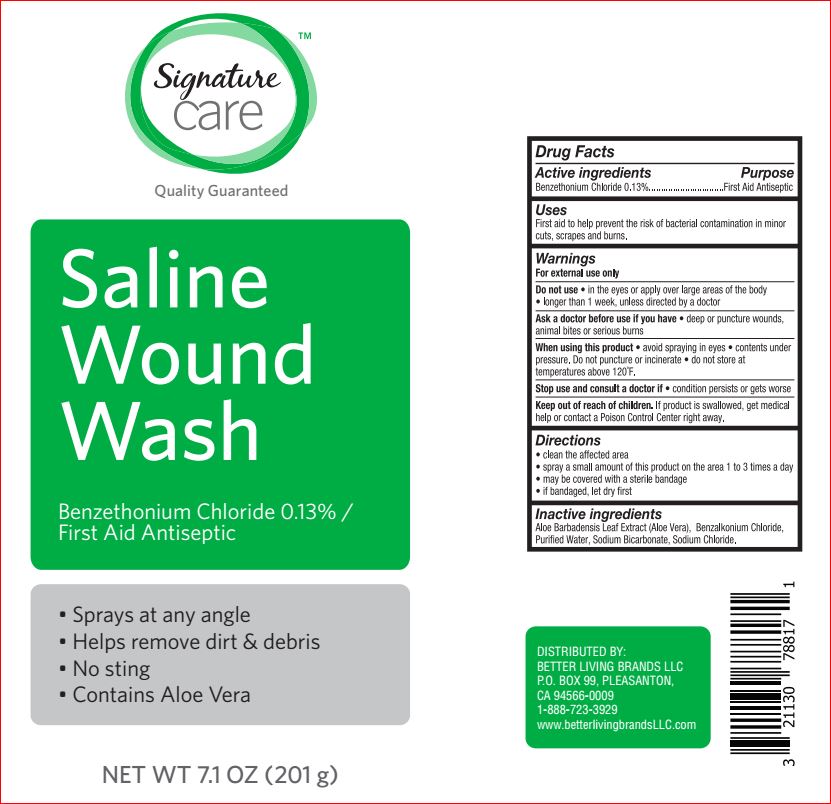 DRUG LABEL: Saline Wound Wash
NDC: 21130-762 | Form: LIQUID
Manufacturer: Better Living
Category: otc | Type: HUMAN OTC DRUG LABEL
Date: 20180131

ACTIVE INGREDIENTS: Benzethonium Chloride 0.1 g/100 g
INACTIVE INGREDIENTS: BENZALKONIUM CHLORIDE; ALOE VERA LEAF; water; SODIUM BICARBONATE; SODIUM CHLORIDE

Drug Facts

Active ingredient Purpose
Benzethonium Chloride 0.13%.........................................................Topical anesthetic

Uses

First aid to help prevent the rick of bacterial contamination in minor cuts, scrapes and burns

Warnings
For external use only.

Do not use in the eyes • longer than 1 week
When using this product avoid spraying in eyes

Do not puncture or incenerate. Contents under pressure. Do not store at temperature above 120F
Stop use and ask a doctor if • condition worsens or persists

Keep out of reach of children. If swallowed, get medical help or contact a Poison Control Center immediately

Directions

- clean the affected area
- spray a small amount of this product on the area 1 to 3 times a day
- may be covered with steriline bandage
- if bandage, let dry first

Inactive ingredients

BENZALKONIUM CHLORIDE

ALOE VERA LEAF

water

SODIUM BICARBONATE

SODIUM CHLORIDE